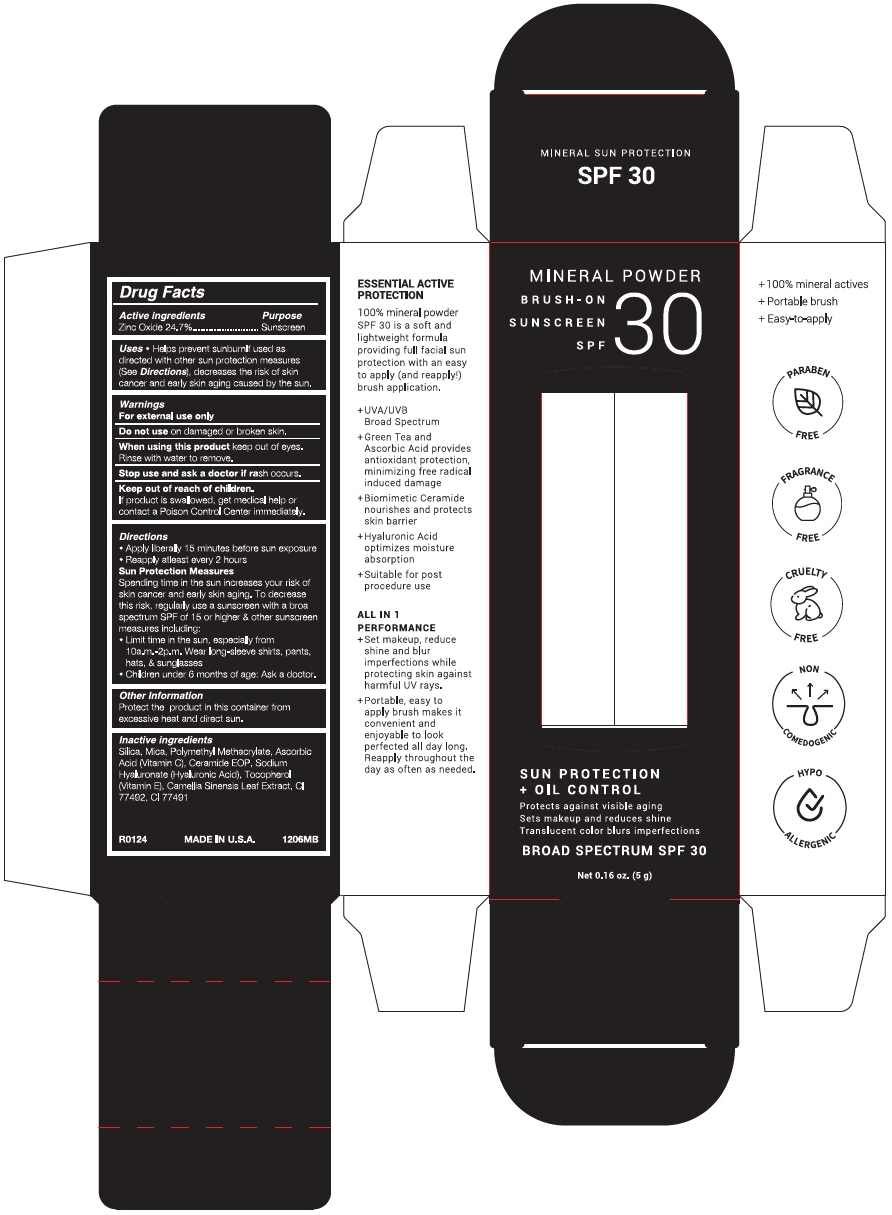 DRUG LABEL: Topix Mineral Finishing Sunscreen
NDC: 51326-206 | Form: POWDER
Manufacturer: Topiderm, Inc
Category: otc | Type: HUMAN OTC DRUG LABEL
Date: 20240418

ACTIVE INGREDIENTS: ZINC OXIDE 241 mg/1 g
INACTIVE INGREDIENTS: SILICON DIOXIDE; MICA; POLY(METHYL METHACRYLATE; 450000 MW); ASCORBIC ACID; CERAMIDE 1; HYALURONATE SODIUM; .ALPHA.-TOCOPHEROL; GREEN TEA LEAF; FERRIC OXIDE YELLOW; FERRIC OXIDE RED

Topix Mineral Finishing Sunscreen
SPF 30

Drug Facts

Active ingredients

Zinc Oxide 24.7%

Purpose

Sunscreen

Uses

- Helps prevent sunburn If used as directed with other sun protection measures (See Directions), decreases the risk of skin cancer and early skin aging caused by the sun.

Warnings

For external use only

Do not use on damaged or broken skin.

When using this product keep out of eyes. Rinse with water to remove.

Stop use and ask a doctor if rash occurs.

Keep out of reach of children.

If product is swallowed, get medical help or contact a Poison Control Center immediately.

Directions

- Apply liberally 15 minutes before sun exposure
- Reapply at least every 2 hours

Sun Protection Measures

Spending time in the sun increases your risk of skin cancer and early skin aging. To decrease this risk, regularly use a sunscreen with a broad spectrum SPF of 15 or higher & other sunscreen measures including:

- Limit time in the sun, especially from 10a.m.-2p.m. Wear long-sleeve shirts, pants, hats, & sunglasses
- Children under 6 months of age: Ask a doctor.

Other Information

Protect the product in this container from excessive heat and direct sun.

Inactive ingredients

Silica, Mica, Polymethyl Methacrylate, Ascorbic Acid (Vitamin C), Ceramide EOP, Sodium Hyaluronate (Hyaluronic Acid), Tocopherol (Vitamin E), Camellia Sinensis Leaf Extract, CI 77492, CI 77491

PRINCIPAL DISPLAY PANEL - 5 g Bottle Box

MINERAL POWDER

BRUSH-ON
SUNSCREEN
SPF
30

SUN PROTECTION
+ OIL CONTROL

Protects against visible aging
Sets makeup and reduces shine
Translucent color blurs imperfections

BROAD SPECTRUM SPF 30

Net 0.16 oz. (5 g)